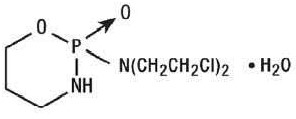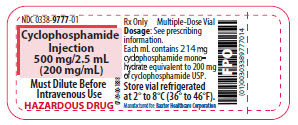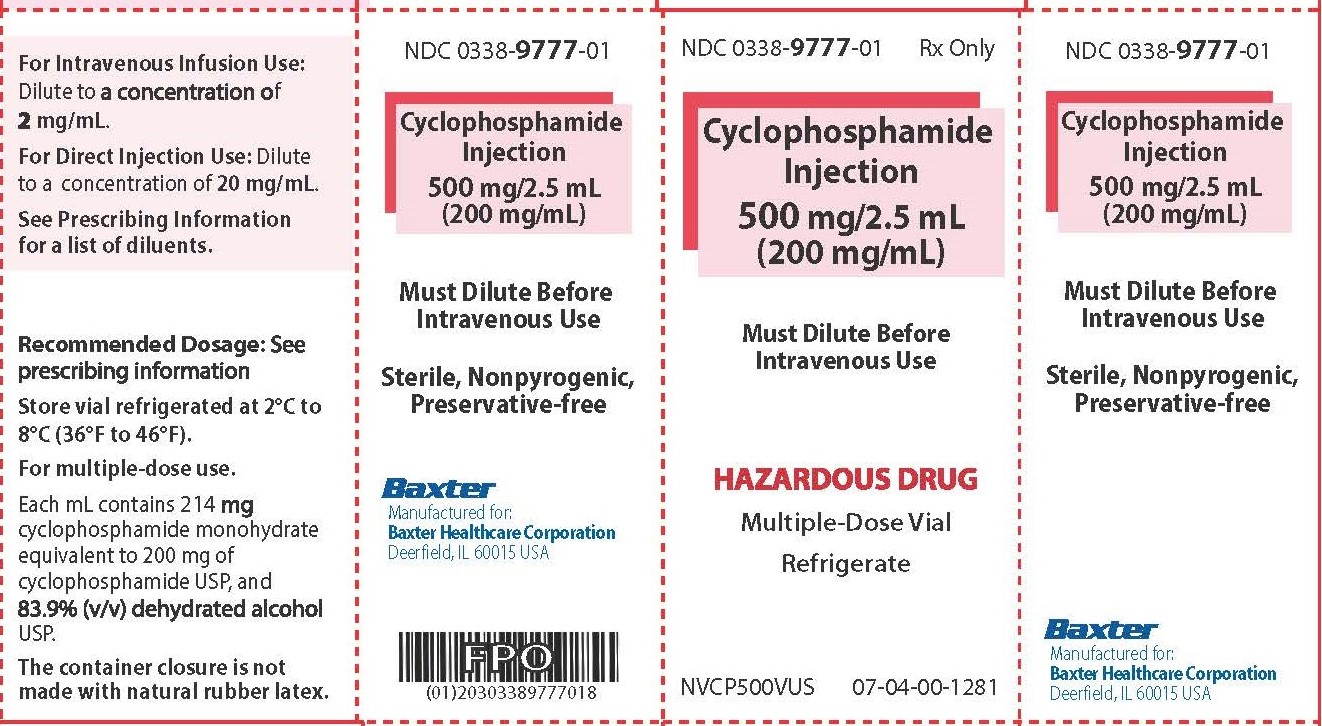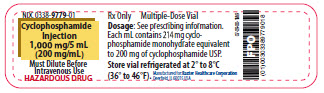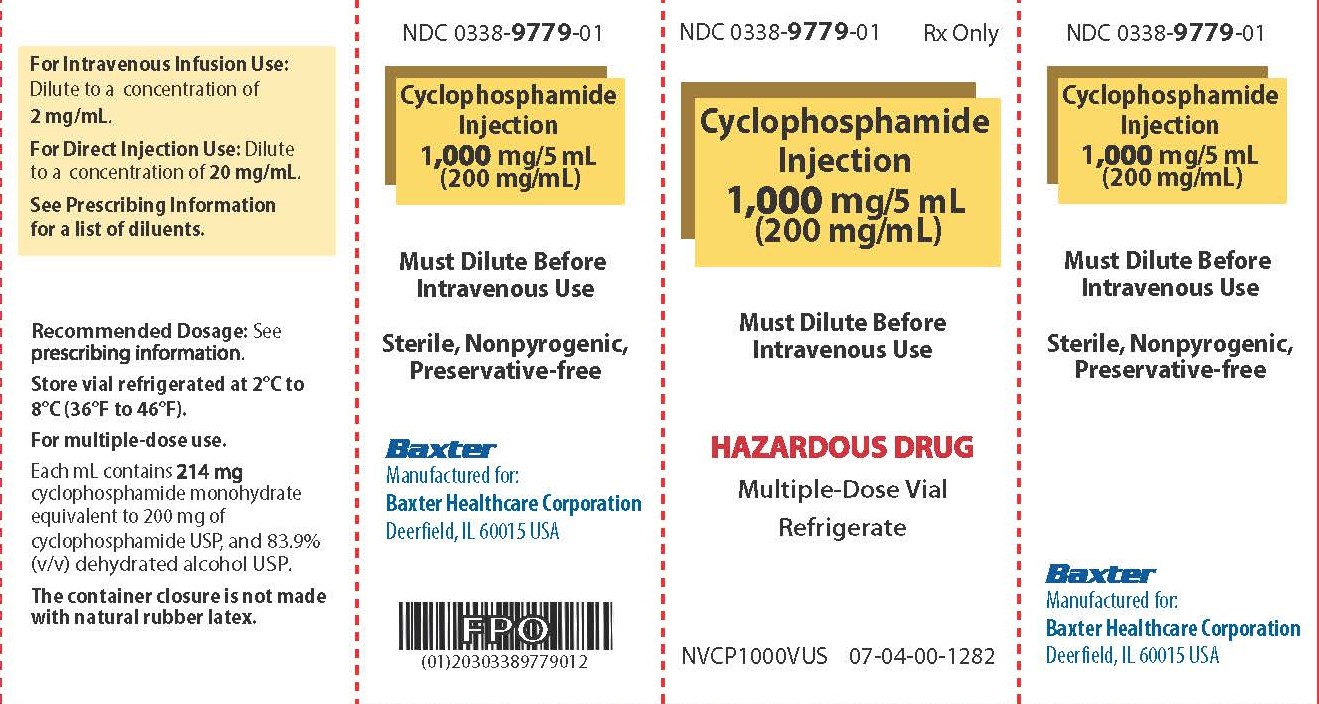 DRUG LABEL: Cyclophosphamide
NDC: 0338-9777 | Form: INJECTION
Manufacturer: Baxter Healthcare Company
Category: prescription | Type: HUMAN PRESCRIPTION DRUG LABEL
Date: 20240410

ACTIVE INGREDIENTS: CYCLOPHOSPHAMIDE 200 mg/1 mL
INACTIVE INGREDIENTS: ALCOHOL; NITROGEN

HIGHLIGHTS OF PRESCRIBING INFORMATION

These highlights do not include all the information needed to use CYCLOPHOSPHAMIDE INJECTION safely and effectively. See full prescribing information for CYCLOPHOSPHAMIDE INJECTION.
CYCLOPHOSPHAMIDE injection, for intravenous use
Initial U.S. Approval: 1959

1 INDICATIONS AND USAGE

Cyclophosphamide Injection is an alkylating drug indicated for treatment of adult and pediatric patients with:

- Malignant Diseases: malignant lymphomas: Hodgkin's disease, lymphocytic lymphoma, mixed-cell type lymphoma, histiocytic lymphoma, Burkitt's lymphoma; multiple myeloma, leukemias, mycosis fungoides, neuroblastoma, adenocarcinoma of ovary, retinoblastoma, breast carcinoma. (1)

2 DOSAGE AND ADMINISTRATION

Malignant Diseases: Adult and Pediatric Patients (2.2)

- Intravenous: Initial course for patients with no hematologic deficiency: 40 mg/kg to 50 mg/kg in divided doses over 2 to 5 days. Other regimens include 10 mg/ kg to 15 mg/ kg given every 7 to 10 days or 3 mg/ kg to 5 mg/ kg twice weekly.
- See full prescribing information for instructions on preparation, handling, and administration. (2.3)

3 DOSAGE FORMS AND STRENGTHS

Injection: 500 mg/2.5 mL (200 mg/mL) and 1,000 mg/5 mL (200 mg/mL) in a multiple-dose vial (3)

4 CONTRAINDICATIONS

- Severe hypersensitivity to cyclophosphamide (4)
- Urinary outflow obstruction (4)

5 WARNINGS AND PRECAUTIONS

- Myelosuppression, Immunosuppression, Bone Marrow Failure and Infections - Severe immunosuppression may lead to serious and sometimes fatal infections. Close hematological monitoring is required. (5.1)
- Urinary Tract and Renal Toxicity - Hemorrhagic cystitis, pyelitis, ureteritis, and hematuria can occur. Exclude or correct any urinary tract obstructions prior to treatment. (5.2)
- Cardiotoxicity - Myocarditis, myopericarditis, pericardial effusion, arrhythmias and congestive heart failure, which may be fatal, have been reported. Monitor patients, especially those with risk factors for cardio toxicity or pre-existing cardiac disease. (5.3)
- Pulmonary Toxicity - Pneumonitis, pulmonary fibrosis and pulmonary veno-occlusive disease leading to respiratory failure may occur. Monitor patients for signs and symptoms of pulmonary toxicity. (5.4)
- Secondary Malignancies - Have been reported in patients treated with cyclophosphamide-containing regimens. (5.5)
- Veno-occlusive Liver Disease - Fatal outcome can occur. (5.6)
- Alcohol Content - The alcohol content in a dose of Cyclophosphamide Injection may affect the central nervous system. This may include impairment of a patient’s ability to drive or use machines immediately after infusion. (5.7)
- Embryo-Fetal Toxicity - Can cause fetal harm. Advise patients of reproductive potential of the potential risk to a fetus and to use effective contraception. (5.8, 8.1, 8.3)

6 ADVERSE REACTIONS

Most common adverse reactions reported are neutropenia, febrile neutropenia, fever, alopecia, nausea, vomiting, and diarrhea. (6.1)

To report SUSPECTED ADVERSE REACTIONS, contact Baxter Healthcare at 1-866-888-2472 or FDA at 1-800-FDA-1088 or www.fda.gov/medwatch.

8 USE IN SPECIFIC POPULATIONS

- Lactation: Advise not to breastfeed. (8.2)
- Renal Patients: Monitor for toxicity in patients with moderate and severe renal impairment. (8.6, 12.3)

FULL PRESCRIBING INFORMATION

1 INDICATIONS AND USAGE

Malignant Diseases

Cyclophosphamide Injection is indicated for the treatment of adult and pediatric patients with:

- malignant lymphomas (Stages III and IV of the Ann Arbor staging system), Hodgkin's disease, lymphocytic lymphoma (nodular or diffuse), mixed-cell type lymphoma, histiocytic lymphoma, Burkitt's lymphoma
- multiple myeloma
- leukemias: chronic lymphocytic leukemia, chronic granulocytic leukemia (it is usually ineffective in acute blastic crisis), acute myelogenous and monocytic leukemia, acute lymphoblastic (stem-cell) leukemia (cyclophosphamide given during remission is effective in prolonging its duration)
- mycosis fungoides (advanced disease)
- neuroblastoma (disseminated disease)
- adenocarcinoma of the ovary
- retinoblastoma
- carcinoma of the breast

Cyclophosphamide, although effective alone in susceptible malignancies, is more frequently used concurrently or sequentially with other antineoplastic drugs.

2 DOSAGE AND ADMINISTRATION

2.1 Important Dosing Information

During or immediately after the administration, adequate amounts of fluid should be ingested or infused to force diuresis in order to reduce the risk of urinary tract toxicity. Therefore, Cyclophosphamide Injection should be administered in the morning.

2.2 Recommended Dosage for Malignant Diseases

Adults and Pediatric Patients

Intravenous

When used as the only oncolytic drug therapy, the initial course of Cyclophosphamide Injection for patients with no hematologic deficiency usually consists of 40 mg/kg to 50 mg/kg given intravenously in divided doses over a period of 2 to 5 days. Other intravenous regimens include 10 mg/kg to 15 mg/kg given every 7 to 10 days or 3 mg/kg to 5 mg/kg twice weekly.

Dosages may also be adjusted based on antitumor activity and/or leukopenia. The total leukocyte count may be used to manage dosage.

When Cyclophosphamide Injection is included in combined cytotoxic regimens, it may be necessary to reduce the dose of Cyclophosphamide Injection as well as that of the other drugs.

2.3 Preparation, Handling and Administration

Cyclophosphamide Injection is a hazardous drug.^1 Follow applicable special handling and disposal procedures. Caution should be exercised when handling and preparing Cyclophosphamide Injection. To minimize the risk of dermal exposure, always wear gloves when handling vials containing Cyclophosphamide Injection.

Cyclophosphamide Injection

Parenteral drug products should be inspected visually for particulate matter and discoloration prior to administration, whenever solution and container permit. Do not use Cyclophosphamide Injection vials if there are signs of particulate matter.

Cyclophosphamide Injection does not contain any antimicrobial preservative and thus care must be taken to assure the sterility of prepared solutions. Use aseptic technique.

For Direct Intravenous Injection

Aseptically withdraw the prescribed dose from the vial. Dilute the prescribed dose of Cyclophosphamide Injection to a concentration of 20 mg per mL by using any of the following diluents:

- 0.9% Sodium Chloride Injection, USP
- 0.45% Sodium Chloride Injection, USP
- 5% Dextrose Injection, USP
- 5% Dextrose and 0.9% Sodium Chloride Injection, USP

Do not use Sterile Water for Injection, USP because it results in a hypotonic solution and should not be injected directly.

For Intravenous Infusion

Aseptically withdraw the prescribed dose from the vial. Dilute the prescribed dose of Cyclophosphamide Injection to a concentration of 2 mg per mL by using any of the following diluents:

- 0.9% Sodium Chloride Injection, USP
- 0.45% Sodium Chloride Injection, USP
- 5% Dextrose Injection, USP
- 5% Dextrose and 0.9% Sodium Chloride Injection, USP

To reduce the likelihood of adverse reactions that appear to be administration rate-dependent (e.g., facial swelling, headache, nasal congestion, scalp burning), Cyclophosphamide Injection should be injected or infused very slowly. Duration of the infusion also should be appropriate for the volume and type of carrier fluid to be infused.

Storage of Diluted Cyclophosphamide Injection Solution:

If not used immediately, for microbiological integrity, cyclophosphamide solutions should be stored as described in Table 1:

Table 1: Storage of Cyclophosphamide Injection Solutions
Diluent | Storage
Diluent | Room Temperature | Refrigerated
Diluted solutions (20 mg/mL)
0.9% Sodium Chloride Injection, USP | up to 24 hrs | up to 6 days
0.45% Sodium Chloride Injection, USP | up to 24 hrs | up to 6 days
5% Dextrose Injection, USP | up to 24 hrs | up to 6 days
5% Dextrose and 0.9% Sodium Chloride Injection, USP | up to 24 hrs | up to 6 days
Diluted Solutions (2 mg/mL)
0.9% Sodium Chloride Injection, USP | up to 24 hrs | up to 6 days
0.45% Sodium Chloride Injection, USP | up to 24 hrs | up to 6 days
5% Dextrose Injection, USP | up to 24 hrs | up to 6 days
5% Dextrose and 0.9% Sodium Chloride Injection, USP | up to 24 hrs | up to 6 days

Storage of Undiluted Cyclophosphamide Injection Solution:

After first use, store partially used multiple-dose vial in the original carton at 2°C to 8°C (36ºF to 46°F) for up to 28 days. Discard unused portion after 28 days.

3 DOSAGE FORMS AND STRENGTHS

Cyclophosphamide Injection is a clear or colorless ready to dilute sterile solution in a multiple-dose vial available in the following presentations:

- 500 mg/2.5 mL (200 mg/mL)
- 1,000 mg/5 mL (200 mg/mL)

4 CONTRAINDICATIONS

Hypersensitivity

Cyclophosphamide is contraindicated in patients who have a history of severe hypersensitivity reactions to it, any of its metabolites, or to other components of the product. Anaphylactic reactions including death have been reported with cyclophosphamide. Possible cross-sensitivity with other alkylating agents can occur.

Urinary Outflow Obstruction

Cyclophosphamide is contraindicated in patients with urinary outflow obstruction [see Warnings and Precautions (5.2)].

5 WARNINGS AND PRECAUTIONS

5.1 Myelosuppression, Immunosuppression, Bone Marrow Failure and Infections

Cyclophosphamide can cause myelosuppression (leukopenia, neutropenia, thrombocytopenia and anemia), bone marrow failure, and severe immunosuppression which may lead to serious and sometimes fatal infections, including sepsis and septic shock. Latent infections can be reactivated [see Adverse Reactions (6.1)].

Antimicrobial prophylaxis may be indicated in certain cases of neutropenia at the discretion of the managing physician. In case of neutropenic fever, antibiotic therapy is indicated. Antimycotics and/or antivirals may also be indicated.

Monitoring of complete blood counts is essential during cyclophosphamide treatment so that the dose can be adjusted, if needed. Cyclophosphamide Injection should not be administered to patients with neutrophils ≤1,500/mm^3 and platelets < 50,000/mm^3. Cyclophosphamide Injection treatment may not be indicated, or should be interrupted, or the dose reduced, in patients who have or who develop a serious infection. G-CSF may be administered to reduce the risks of neutropenia complications associated with cyclophosphamide use. Primary and secondary prophylaxis with G-CSF should be considered in all patients considered to be at increased risk for neutropenia complications. The nadirs of the reduction in leukocyte count and thrombocyte count are usually reached in weeks 1 and 2 of treatment. Peripheral blood cell counts are expected to normalize after approximately 20 days. Bone marrow failure has been reported. Severe myelosuppression may be expected particularly in patients pretreated with and/or receiving concomitant chemotherapy and/or radiation therapy.

5.2 Urinary Tract and Renal Toxicity

Hemorrhagic cystitis, pyelitis, ureteritis, and hematuria have been reported with cyclophosphamide. Medical and/or surgical supportive treatment may be required to treat protracted cases of severe hemorrhagic cystitis. Discontinue cyclophosphamide therapy in case of severe hemorrhagic cystitis. Urotoxicity (bladder ulceration, necrosis, fibrosis, contracture and secondary cancer) may require interruption of cyclophosphamide treatment or cystectomy. Urotoxicity can be fatal. Urotoxicity can occur with short-term or long-term use of cyclophosphamide.

Before starting treatment, exclude or correct any urinary tract obstructions [see Contraindications (4)]. Urinary sediment should be checked regularly for the presence of erythrocytes and other signs of urotoxicity and/or nephrotoxicity. Cyclophosphamide Injection should be used with caution, if at all, in patients with active urinary tract infections. Aggressive hydration with forced diuresis and frequent bladder emptying can reduce the frequency and severity of bladder toxicity. Mesna has been used to prevent severe bladder toxicity.

5.3 Cardiotoxicity

Myocarditis, myopericarditis, pericardial effusion including cardiac tamponade, and congestive heart failure, which may be fatal, have been reported with cyclophosphamide therapy.

Supraventricular arrhythmias (including atrial fibrillation and flutter) and ventricular arrhythmias (including severe QT prolongation associated with ventricular tachyarrhythmia) have been reported after treatment with regimens that included cyclophosphamide.

The risk of cardiotoxicity may be increased with high doses of cyclophosphamide, in patients with advanced age, and in patients with previous radiation treatment to the cardiac region and/or previous or concomitant treatment with other cardiotoxic agents.

Particular caution is necessary in patients with risk factors for cardiotoxicity and in patients with pre- existing cardiac disease.

Monitor patients with risk factors for cardiotoxicity and with pre-existing cardiac disease.

5.4 Pulmonary Toxicity

Pneumonitis, pulmonary fibrosis, pulmonary veno-occlusive disease and other forms of pulmonary toxicity leading to respiratory failure have been reported during and following treatment with cyclophosphamide. Late onset pneumonitis (greater than 6 months after start of cyclophosphamide) appears to be associated with increased mortality. Pneumonitis may develop years after treatment with cyclophosphamide.

Monitor patients for signs and symptoms of pulmonary toxicity.

5.5 Secondary Malignancies

Cyclophosphamide is genotoxic [see Nonclinical Toxicology (13.1)]. Secondary malignancies (urinary tract cancer, myelodysplasia, acute leukemias, lymphomas, thyroid cancer, and sarcomas) have been reported in patients treated with cyclophosphamide-containing regimens. The risk of bladder cancer may be reduced by prevention of hemorrhagic cystitis.

5.6 Veno-occlusive Liver Disease

Veno-occlusive liver disease (VOD) including fatal outcome has been reported in patients receiving cyclophosphamide-containing regimens. A cytoreductive regimen in preparation for bone marrow transplantation that consists of cyclophosphamide in combination with whole-body irradiation, busulfan, or other agents has been identified as a major risk factor. VOD has also been reported to develop gradually in patients receiving long-term low-dose immunosuppressive doses of cyclophosphamide. Other risk factors predisposing to the development of VOD include preexisting disturbances of hepatic function, previous radiation therapy of the abdomen, and a low performance status.

5.7 Alcohol Content

The alcohol content in a dose of Cyclophosphamide Injection may affect the central nervous system and should be taken into account for patients in whom alcohol intake should be avoided or minimized. Consideration should be given to the alcohol content in Cyclophosphamide Injection on the ability to drive or use machines immediately after the infusion.

Each administration of Cyclophosphamide Injection at 50 mg per kg delivers 0.166 g/kg of ethanol over 2 to 5 days. For a 75 kg patient this would deliver 12.45 grams of ethanol over 2 to 5 days [see Description (11)]. Other cyclophosphamide products may have a different amount of alcohol or no alcohol.

5.8 Embryo-Fetal Toxicity

Based on its mechanism of action and published reports of effects in pregnant patients or animals, Cyclophosphamide Injection can cause fetal harm when administered to a pregnant woman [see Use in Specific Populations (8.1), Clinical Pharmacology (12.1) and Nonclinical Toxicology (13.1)]. Exposure to cyclophosphamide during pregnancy may cause birth defects, miscarriage, fetal growth retardation, and fetotoxic effects in the newborn. Cyclophosphamide is teratogenic and embryo-fetal toxic in mice, rats, rabbits and monkeys.

Advise pregnant women and females of reproductive potential of the potential risk to a fetus [see Use in Specific Populations (8.1)]. Advise females of reproductive potential to use effective contraception during treatment with Cyclophosphamide Injection and for up to 1 year after completion of therapy. Advise male patients with female partners of reproductive potential to use effective contraception during treatment with Cyclophosphamide Injection and for 4 months after completion of therapy [see Use in Specific Populations (8.1, 8.3)].

5.9 Infertility

Male and female reproductive function and fertility may be impaired in patients being treated with Cyclophosphamide Injection. Cyclophosphamide interferes with oogenesis and spermatogenesis. It may cause sterility in both sexes. Development of sterility appears to depend on the dose of cyclophosphamide, duration of therapy, and the state of gonadal function at the time of treatment. Cyclophosphamide-induced sterility may be irreversible in some patients. Advise patients on the potential risks for infertility [see Use in Specific Populations (8.3 and 8.4)].

5.10 Impairment of Wound Healing

Cyclophosphamide may interfere with normal wound healing.

5.11 Hyponatremia

Hyponatremia associated with increased total body water, acute water intoxication, and a syndrome resembling SIADH (syndrome of inappropriate secretion of antidiuretic hormone), which may be fatal, has been reported.

6 ADVERSE REACTIONS

The following adverse reactions are discussed in more detail in other sections of the labeling.

- Hypersensitivity [see Contraindications (4)]
- Myelosuppression, Immunosuppression, Bone Marrow Failure, and Infections [see Warnings and Precautions (5.1)]
- Urinary Tract and Renal Toxicity [see Warnings and Precautions (5.2)]
- Cardiotoxicity [see Warnings and Precautions (5.3)]
- Pulmonary Toxicity [see Warnings and Precautions (5.4)]
- Secondary Malignancies [see Warnings and Precautions (5.5)]
- Veno-occlusive Liver Disease [see Warnings and Precautions (5.6)]
- Alcohol Content [see Warnings and Precautions (5.7)]
- Infertility [see Warnings and Precautions (5.9) and Use in Specific Populations (8.3 and 8.4)]
- Impaired Wound Healing [see Warnings and Precautions (5.10)]
- Hyponatremia [see Warnings and Precautions (5.11)]

6.1 Clinical Trials and Postmarketing Experience

The following adverse reactions associated with the use of cyclophosphamide were identified in clinical studies or post-marketing reports. Because some of these reactions were reported voluntarily from a population of uncertain size, it is not always possible to reliably estimate their frequency or establish a causal relationship to drug exposure. The most common adverse reactions were neutropenia, febrile neutropenia, fever, alopecia, nausea, vomiting, and diarrhea.

Cardiac: cardiac arrest, ventricular fibrillation, ventricular tachycardia, cardiogenic shock, pericardial effusion (progressing to cardiac tamponade), myocardial hemorrhage, myocardial infarction, cardiac failure (including fatal outcomes), cardiomyopathy, myocarditis, pericarditis, carditis, atrial fibrillation, supraventricular arrhythmia, ventricular arrhythmia, bradycardia, tachycardia, palpitations, QT prolongation.

Congenital, Familial and Genetic: intra-uterine death, fetal malformation, fetal growth retardation, fetal toxicity (including myelosuppression, gastroenteritis).

Ear and Labyrinth: deafness, hearing impaired, tinnitus.

Endocrine: water intoxication.

Eye: visual impairment, conjunctivitis, lacrimation.

Gastrointestinal: gastrointestinal hemorrhage, acute pancreatitis, colitis, enteritis, cecitis, stomatitis, constipation, parotid gland inflammation, nausea, vomiting, diarrhea.

General Disorders and Administrative Site Conditions: multiorgan failure, general physical deterioration, influenza-like illness, injection/infusion site reactions (thrombosis, necrosis, phlebitis, inflammation, pain, swelling, erythema), pyrexia, edema, chest pain, mucosal inflammation, asthenia, pain, chills, fatigue, malaise, headache, febrile neutropenia.

Hematologic: myelosuppression, bone marrow failure, disseminated intravascular coagulation and hemolytic uremic syndrome (with thrombotic microangiopathy).

Hepatic: veno-occlusive liver disease, cholestatic hepatitis, cytolytic hepatitis, hepatitis, cholestasis; hepatotoxicity with hepatic failure, hepatic encephalopathy, ascites, hepatomegaly, blood bilirubin increased, hepatic function abnormal, hepatic enzymes increased.

Immune: immunosuppression, anaphylactic shock and hypersensitivity reaction.

Infections: The following manifestations have been associated with myelosuppression and immunosuppression caused by cyclophosphamide: increased risk for and severity of pneumonias (including fatal outcomes), other bacterial, fungal, viral, protozoal and, parasitic infections; reactivation of latent infections, (including viral hepatitis, tuberculosis), Pneumocystis jiroveci, herpes zoster, Strongyloides, sepsis and septic shock.

Investigations: blood lactate dehydrogenase increased, C-reactive protein increased.

Metabolism and Nutrition: hyponatremia, fluid retention, blood glucose increased, blood glucose decreased.

Musculoskeletal and Connective Tissue: rhabdomyolysis, scleroderma, muscle spasms, myalgia, arthralgia.

Neoplasms: acute leukemia, myelodysplastic syndrome, lymphoma, sarcomas, renal cell carcinoma, renal pelvis cancer, bladder cancer, ureteric cancer, thyroid cancer.

Nervous System: encephalopathy, convulsion, dizziness, neurotoxicity has been reported and manifested as reversible posterior leukoencephalopathy syndrome, myelopathy, peripheral neuropathy, polyneuropathy, neuralgia, dysesthesia, hypoesthesia, paresthesia, tremor, dysgeusia, hypogeusia, parosmia.

Pregnancy: premature labor.

Psychiatric: confusional state.

Renal and Urinary: renal failure, renal tubular disorder, renal impairment, nephropathy toxic, hemorrhagic cystitis, bladder necrosis, cystitis ulcerative, bladder contracture, hematuria, nephrogenic diabetes insipidus, atypical urinary bladder epithelial cells.

Reproductive System: infertility, ovarian failure, ovarian disorder, amenorrhea, oligomenorrhea, testicular atrophy, azoospermia, oligospermia.

Respiratory: pulmonary veno-occlusive disease, acute respiratory distress syndrome, interstitial lung disease as manifested by respiratory failure (including fatal outcomes), obliterative bronchiolitis, organizing pneumonia, alveolitis allergic, pneumonitis, pulmonary hemorrhage; respiratory distress, pulmonary hypertension, pulmonary edema, pleural effusion, bronchospasm, dyspnea, hypoxia, cough, nasal congestion, nasal discomfort, oropharyngeal pain, rhinorrhea.

Skin and Subcutaneous Tissue: toxic epidermal necrolysis, Stevens-Johnson syndrome, erythema multiforme, palmar-plantar erythrodysesthesia syndrome, radiation recall dermatitis, toxic skin eruption, urticaria, dermatitis, blister, pruritus, erythema, nail disorder, facial swelling, hyperhidrosis, alopecia.

Tumor lysis syndrome: like other cytotoxic drugs, cyclophosphamide may induce tumor-lysis syndrome and hyperuricemia in patients with rapidly growing tumors.

Vascular: pulmonary embolism, venous thrombosis, vasculitis, peripheral ischemia, hypertension, hypotension, flushing, hot flush.

7 DRUG INTERACTIONS

7.1 Effect of Other Drugs on Cyclophosphamide Exposure

Protease Inhibitors

Cyclophosphamide is a pro-drug that is activated by cytochrome P450s [see Clinical Pharmacology (12.3)].

Concomitant use of protease inhibitors may increase the concentration of cytotoxic metabolites. Use of protease inhibitor-based regimens was found to be associated with a higher Incidence of infections and neutropenia in patients receiving cyclophosphamide, doxorubicin, and etoposide (CDE) than use of a Non-Nucleoside Reverse Transcriptase Inhibitor-based regimen.

7.2 Drugs that Can Potentiate Cyclophosphamide Toxicities

Combined or sequential use of Cyclophosphamide Injection and other drugs or agents with similar toxicities to Cyclophosphamide Injection and can potentiate these effects and are listed in Table 2.

Table 2: Drugs that Can Potentiate Cyclophosphamide Toxicities
Toxicity | Drug or other treatment
Increased hematotoxicity and/or immunosuppression | - ACE inhibitors: ACE inhibitors can cause leukopenia. - Natalizumab - Paclitaxel: Increased hematotoxicity has been reported when cyclophosphamide was administered after paclitaxel infusion. - Thiazide diuretics - Zidovudine
Increased cardiotoxicity | - Anthracyclines - Cytarabine - Pentostatin - Radiation therapy of the cardiac region - Trastuzumab
Increased pulmonary toxicity | - Amiodarone - G-CSF, GM-CSF (granulocyte colony-stimulating factor, granulocyte macrophage colony-stimulating factor)
Increased nephrotoxicity | - Amphotericin B - Indomethacin: Acute water intoxication has been reported with concomitant use of indomethacin
Increase in other toxicities: | - Azathioprine: Increased risk of hepatotoxicity (liver necrosis) - Busulfan: Increased incidence of hepatic veno-occlusive disease and mucositis has been reported. - Protease inhibitors: Increased incidence of mucositis
Increased risk of hemorrhagic cystitis | - Radiation treatment: Increased risk of hemorrhagic cystitis may result from a combined effect of cyclophosphamide and past or concomitant radiation treatment.

7.3 Effect of Cyclophosphamide With Other Drugs

Etanercept

A higher incidence of non-cutaneous malignant solid tumors in patients with Wegener’s granulomatosis occurred with the addition of etanercept to cyclophosphamide treatment.

Metronidazole

Acute encephalopathy has been reported in a patient receiving cyclophosphamide and metronidazole. In an animal study, the combination of cyclophosphamide with metronidazole was associated with increased cyclophosphamide toxicity.

Tamoxifen

Concomitant use of tamoxifen and chemotherapy may increase the risk of thromboembolic complications.

Coumarins

Both increased and decreased warfarin effect have been reported in patients receiving warfarin and cyclophosphamide.

Cyclosporine

Lower serum concentrations of cyclosporine have been observed in patients receiving a combination of cyclophosphamide and cyclosporine than in patients receiving only cyclosporine. This interaction may result in an increased incidence of graft-versus-host disease.

Depolarizing muscle relaxants

If a patient has been treated with cyclophosphamide within 10 days of general anesthesia, alert the anesthesiologist.

Cyclophosphamide treatment causes a marked and persistent inhibition of cholinesterase activity. Prolonged apnea may occur with concurrent depolarizing muscle relaxants (e.g., succinylcholine).

8 USE IN SPECIFIC POPULATIONS

8.1 Pregnancy

Risk Summary

Based on its mechanism of action and published reports of effects in pregnant patients or animals, Cyclophosphamide Injection can cause fetal harm when administered to a pregnant woman [see Clinical Pharmacology (12.1) and Nonclinical Toxicology (13.1)]. Exposure to cyclophosphamide during pregnancy may cause fetal malformations, miscarriage, fetal growth retardation, and toxic effects in the newborn [see Data]. Cyclophosphamide is teratogenic and embryo-fetal toxic in mice, rats, rabbits and monkeys [see Data]. Advise pregnant women and females of reproductive potential of the potential risk to the fetus.

The estimated background risk of major birth defects and miscarriage for the indicated population is unknown. In the U.S. general population, the estimated background risk of major birth defects is 2% - 4% and of miscarriage is 15% - 20% of clinically recognized pregnancies.

Data

Human Data

Malformations of the skeleton, palate, limbs and eyes as well as miscarriage have been reported after exposure to cyclophosphamide in the first trimester. Fetal growth retardation and toxic effects manifesting in the newborn, including leukopenia, anemia, pancytopenia, severe bone marrow hypoplasia, and gastroenteritis have been reported after exposure to cyclophosphamide.

Animal Data

Administration of cyclophosphamide to pregnant mice, rats, rabbits and monkeys during the period of organogenesis at doses at or below the dose in patients based on body surface area resulted in various malformations, which included neural tube defects, limb and digit defects and other skeletal anomalies, cleft lip and palate, and reduced skeletal ossification.

8.2 Lactation

Risk Summary

Cyclophosphamide is present in breast milk. Neutropenia, thrombocytopenia, low hemoglobin, and diarrhea have been reported in infants breast fed by women treated with cyclophosphamide. Because of the potential for serious adverse reactions in a breastfed child, advise lactating women not to breastfeed during treatment with Cyclophosphamide Injection and for 1 week after the last dose.

8.3 Females and Males of Reproductive Potential

Cyclophosphamide Injection can cause fetal harm when administered to a pregnant woman [see Use in Specific Populations (8.1)].

Pregnancy Testing

Verify the pregnancy status of females of reproductive potential prior to the initiation of Cyclophosphamide Injection [see Use in Specific Populations (8.1)].

Contraception

Females

Advise females of reproductive potential to use effective contraception during treatment with Cyclophosphamide Injection and for up to 1 year after completion of therapy [see Use in Specific Populations (8.1)].

Males

Based on findings in genetic toxicity and animal reproduction studies, advise male patients with female partners of reproductive potential to use effective contraception during treatment with Cyclophosphamide Injection and for 4 months after completion of therapy [see Use in Specific Populations (8.1) and Nonclinical Toxicology (13.1)].

Infertility

Females

Amenorrhea, transient or permanent, associated with decreased estrogen and increased gonadotropin secretion develops in a proportion of women treated with cyclophosphamide. Affected patients generally resume regular menses within a few months after cessation of therapy. The risk of premature menopause with cyclophosphamide increases with age. Oligomenorrhea has also been reported in association with cyclophosphamide treatment.

Animal data suggest an increased risk of failed pregnancy and malformations may persist after discontinuation of cyclophosphamide as long as oocytes/follicles exist that were exposed to cyclophosphamide during any of their maturation phases. The exact duration of follicular development in humans is not known but may be longer than 12 months [see Nonclinical Toxicology (13.1)].

Males

Men treated with cyclophosphamide may develop oligospermia or azoospermia which are normally associated with increased gonadotropin but normal testosterone secretion.

8.4 Pediatric Use

The safety and effectiveness of Cyclophosphamide Injection have been established in pediatric patients and information on this use is discussed throughout the labeling.

The alcohol content of Cyclophosphamide Injection should be taken into account when given to pediatric patients [see Warnings and Precautions (5.7)].

Pre-pubescent girls treated with cyclophosphamide generally develop secondary sexual characteristics normally and have regular menses. Ovarian fibrosis with apparently complete loss of germ cells after prolonged cyclophosphamide treatment in late pre-pubescence has been reported. Girls treated with cyclophosphamide who have retained ovarian function after completing treatment are at increased risk of developing premature menopause.

Pre-pubescent boys treated with cyclophosphamide develop secondary sexual characteristics normally, but may have oligospermia or azoospermia and increased gonadotropin secretion. Some degree of testicular atrophy may occur. Cyclophosphamide-induced azoospermia is reversible in some patients, though the reversibility may not occur for several years after cessation of therapy.

8.5 Geriatric Use

There is insufficient data from clinical studies of cyclophosphamide available for patients 65 years of age and older to determine whether they respond differently than younger patients. In general, dose selection for an elderly patient should be cautious, usually starting at the low end of the dosing range, reflecting the greater frequency of decreased hepatic, renal, or cardiac functioning, and of concomitant disease or other drug therapy.

8.6 Renal Impairment

In patients with severe renal impairment, decreased renal excretion may result in increased plasma levels of cyclophosphamide and its metabolites. This may result in increased toxicity [see Clinical Pharmacology (12.3)]. Monitor patients with severe renal impairment (CLcr=10 mL/min to 24 mL/min) for signs and symptoms of toxicity.

Cyclophosphamide and its metabolites are dialyzable although there are probably quantitative differences depending upon the dialysis system being used. Use of a consistent interval between cyclophosphamide administration and dialysis should be considered in patients requiring dialysis.

8.7 Hepatic Impairment

Patients with severe hepatic impairment have reduced conversion of cyclophosphamide to the active 4- hydroxyl metabolite, potentially reducing efficacy [see Clinical Pharmacology (12.3)].

The alcohol content of Cyclophosphamide Injection should be taken into account when given to patients with hepatic impairment [see Warnings and Precautions (5.7)].

10 OVERDOSAGE

No specific antidote for cyclophosphamide is known.

Overdosage should be managed with supportive measures, including appropriate treatment for any concurrent infection, myelosuppression, or cardiac toxicity should it occur.

Serious consequences of overdosage include manifestations of dose dependent toxicities such as myelosuppression, urotoxicity, cardiotoxicity (including cardiac failure), veno-occlusive hepatic disease, and stomatitis [see Warnings and Precautions (5.1, 5.2, 5.3, and 5.6)].

Patients who received an overdose should be closely monitored for the development of toxicities, and hematologic toxicity in particular.

Cyclophosphamide and its metabolites are dialyzable. Therefore, rapid hemodialysis is indicated when treating any suicidal or accidental overdose or intoxication.

Cystitis prophylaxis with mesna may be helpful in preventing or limiting urotoxic effects with cyclophosphamide overdose.

11 DESCRIPTION

Cyclophosphamide is an alkylating drug. It is an antineoplastic drug chemically related to the nitrogen mustards. The chemical name for cyclophosphamide is 2-[bis(2-chloroethyl)amino]tetrahydro-2H-1,3,2-oxazaphosphorine 2-oxide monohydrate, and has the following structural formula:

Cyclophosphamide has a molecular formula of C7H15Cl2N2O2P•H2O and a molecular weight of 279.1 g/mol. Cyclophosphamide is soluble in water, saline, or ethanol.

Cyclophosphamide Injection is a 200 mg/mL sterile clear colorless solution for intravenous use and is available as 500 mg and 1,000 mg strength vials.

- 500 mg vial contains 534.5 mg cyclophosphamide monohydrate equivalent to 500 mg cyclophosphamide and 83.9% (v/v) dehydrated alcohol.
- 1,000 mg vial contains 1,069 mg cyclophosphamide monohydrate equivalent to 1,000 mg cyclophosphamide and 83.9% (v/v) dehydrated alcohol.

12 CLINICAL PHARMACOLOGY

12.1 Mechanism of Action

The mechanism of action has not been fully characterized. However, cross-linking of tumor cell DNA may be involved.

The active alkylating metabolites of cyclophosphamide interfere with the growth of susceptible rapidly proliferating malignant cells.

12.2 Pharmacodynamics

Cyclophosphamide exposure-response relationships and the time course of pharmacodynamic response have not been fully characterized.

12.3 Pharmacokinetics

Pharmacokinetics are linear over the dose range used clinically.

Distribution

Cyclophosphamide volume of distribution approximates total body water (30 to 50 L). Cyclophosphamide is approximately 20% protein bound, with no dose dependent changes. Some metabolites are greater than 60% protein bound.

Elimination

The cyclophosphamide elimination half-life ranges from 3 to 12 hours with total body clearance (CL) values of 4 to 5.6 L/h following IV administration. Cyclophosphamide appears to induce its own metabolism. This auto-induction results in an increase in the total clearance, increased formation of active 4-hydroxyl metabolites and shortened elimination half-life values following repeated administration at 12- to 24-hour interval.

When cyclophosphamide was administered at 4.0 g/m^2 (approximately 2 times the approved recommended dosage) over a 90-minutes infusion, saturable elimination in parallel with first-order renal elimination describe the kinetics of the drug.

Metabolism

The liver is the major site of cyclophosphamide activation. Approximately 75% of the administered dose of cyclophosphamide is activated by hepatic microsomal cytochrome P450s including CYP2A6, 2B6, 3A4, 3A5, 2C9, 2C18 and 2C19, with 2B6 displaying the highest 4-hydroxylase activity.

Cyclophosphamide is activated to form 4-hydroxycyclophosphamide, which is in equilibrium with its ring-open tautomer aldophosphamide. 4-hydroxycyclophosphamide and aldophosphamide can undergo further oxidation by aldehyde dehydrogenases to form the inactive metabolites 4-ketocyclophosphamide and carboxyphosphamide, respectively. Aldophosphamide can undergo β-elimination to form active metabolites phosphoramide mustard and acrolein. This spontaneous conversion can be catalyzed by albumin and other proteins. Less than 5% of cyclophosphamide may be directly detoxified by side chain oxidation, leading to the formation of inactive metabolites 2-dechloroethylcyclophosphamide. At high doses, the fraction of parent compound cleared by 4-hydroxylation is reduced resulting in non-linear elimination of cyclophosphamide in patients.

Excretion

Cyclophosphamide is primarily excreted as metabolites. 10 to 20% is excreted unchanged in the urine and 4% is excreted in the bile following IV administration.

Specific Populations

Renal Impairment

Cyclophosphamide exposure increased as the renal function decreased following one-hour intravenous infusion to renally impaired patients. Mean dose-corrected cyclophosphamide AUC increased by 38% in the moderate renal group, (Creatinine clearance (CLcr of 25 to 50 mL/min), by 64% in the severe renal group (CLcr of 10 to 24 mL/min) and by 23% in the hemodialysis group (CLcr of < 10mL/min) compared to the control group.

Cyclophosphamide is dialyzable. Dialysis clearance calculated by arterial-venous difference and actual drug recovery in dialysate averaged 104 mL/min, which is in the range of the metabolic clearance of 95 mL/min for the drug. A mean of 37% of the administered dose of cyclophosphamide was removed during hemodialysis. The elimination half- life (t1/2) was 3.3 hours in patients during hemodialysis, a 49% reduction of the 6.5 hours to the elimination half-life reported in uremic patients.

Hepatic Impairment

Total body clearance (CL) of cyclophosphamide is decreased by 40% in patients with severe hepatic impairment and elimination half-life (t½) is prolonged by 64%. Mean CL and t½ were 45 ± 8.6 L/kg and 12.5 ± 1.0 hours respectively, in patients with severe hepatic impairment and 63 ± 7.6 L/kg and 7.6 ± 1.4 hours respectively in the control group.

13 NONCLINICAL TOXICOLOGY

13.1 Carcinogenesis, Mutagenesis, Impairment of Fertility

Cyclophosphamide administered by different routes, including intravenous, subcutaneous or intraperitoneal injection, or in drinking water, caused tumors in both mice and rats. In addition to leukemia and lymphoma, benign and malignant tumors were found at various tissue sites, including urinary bladder, mammary gland, lung, liver, and injection site [see Warnings and Precautions (5.5)].

Cyclophosphamide was mutagenic and clastogenic in multiple in vitro and in vivo genetic toxicology studies.

Cyclophosphamide is genotoxic in male and female germ cells. Animal data indicate that exposure of oocytes to cyclophosphamide during follicular development may result in a decreased rate of implantations and viable pregnancies, and in an increased risk of malformations. Male mice and rats treated with cyclophosphamide show alterations in male reproductive organs (e.g., decreased weights, atrophy, changes in spermatogenesis), and decreases in reproductive potential (e.g., decreased implantations and increased post-implantation loss) and increases in fetal malformations when mated with untreated females [see Use in Specific Populations (8.3)].

15 REFERENCES

1. OSHA Hazardous drugs. OSHA. http://www.osha.gov/SLTC/hazardousdrugs/index.html

16 HOW SUPPLIED/STORAGE AND HANDLING

Cyclophosphamide Injection is a 200 mg/mL clear or colorless ready-to-dilute sterile solution containing cyclophosphamide, USP.

Cyclophosphamide Injection

NDC Number | Presentation | Pack Factor
0338-9777-01 | 500 mg per 2.5 mL Multiple-Dose Vial | 1 vial per carton
0338-9779-01 | 1,000 mg per 5 mL Multiple-Dose Vial | 1 vial per carton

The container closure is not made with natural rubber latex.

Store the vials refrigerated at 2°C to 8°C (36°F to 46°F).

Cyclophosphamide is a hazardous product. Follow special handling and disposal procedures. ^1

17 PATIENT COUNSELING INFORMATION

Advise the patient of the following:

Myelosuppression, Immunosuppression, and Infections

Inform patients of the possibility of myelosuppression, immunosuppression, and infections. Explain the need for routine blood cell counts. Instruct patients to monitor their temperature frequently and immediately report any occurrence of fever [see Warnings and Precautions (5.1)].

Urinary Tract and Renal Toxicity

Advise the patient to report urinary symptoms (patients should report if their urine has turned a pink or red color) and the need for increasing fluid intake and frequent voiding [see Warnings and Precautions (5.2)].

Cardiotoxicity

Advise patients to contact a health care professional immediately for any of the following: new onset or worsening shortness of breath, cough, swelling of the ankles/legs, palpitations, weight gain of more than 5 pounds in 24 hours, dizziness or loss of consciousness [see Warnings and Precautions (5.3)].

Pulmonary Toxicity

Warn patients of the possibility of developing non-infectious pneumonitis. Advise patients to report promptly any new or worsening respiratory symptoms [see Warnings and Precautions (5.4)].

Alcohol Content

Explain to patients the possible effects of the alcohol content in Cyclophosphamide Injection, including possible effects on central nervous system. Patients in whom alcohol should be avoided or minimized should consider the alcohol content of Cyclophosphamide Injection. Alcohol could impair their ability to drive or use machines immediately after infusion [see Warnings and Precautions (5.7)].

Embryo-Fetal Toxicity

Inform female patients of the risk to a fetus and potential loss of the pregnancy. Advise females to inform their healthcare provider of a known or suspected pregnancy [see Warnings and Precautions (5.8) and Use in Specific Populations (8.1)].

Advise females of reproductive potential to use effective contraception during treatment and for up to 1 year after completion of therapy [see Warning and Precautions (5.8) and Use in Specific Populations (8.1, 8.3)].

Advise male patients with female partners of reproductive potential to use effective contraception during treatment and for 4 months after completion of therapy [see Warnings and Precautions (5.8) and Use in Specific Populations (8.1, 8.3)].

Lactation

Advise lactating women not to breastfeed during treatment and for 1 week after the last dose of Cyclophosphamide Injection [see Use in Specific Populations (8.2)].

Infertility

Advise males and females of reproductive potential that Cyclophosphamide Injection may impair fertility [see Warnings and Precautions (5.9) and Use in Specific Populations (8.3, 8.4)].

Common Adverse Reactions

Explain to patients that side effects such as nausea, vomiting, stomatitis, impaired wound healing, amenorrhea, premature menopause, sterility and hair loss may be associated with cyclophosphamide administration. Other undesirable effects (including, e.g., dizziness, blurred vision, visual impairment) could affect the ability to drive or use machines [see Adverse Reactions (6.1)].

Manufactured for:

Baxter Healthcare Corporation

Deerfield, IL 60015 USA

Baxter is a registered trademark of Baxter International Inc.

Product of USA

07-19-00-7612

PACKAGE/LABEL PRINCIPAL DISPLAY PANEL

Container Label

NDC 0338-9777-01

Cyclophosphamide
Injection
500 mg/2.5 mL
(200 mg/mL)

Must Dilute Before
Intravenous Use

HAZARDOUS DRUG

Rx Only Multiple Dose Vial

Dosage: See prescribing
information.
Each mL contains 214 mg
cyclophosphamide mono-
hydrate equivalent to 200 mg
of cyclophosphamide USP.

Store vial refrigerated
at 2° to 8°C (36° to 46°F).

Manufactured for:
Baxter Healthcare Corporation

FPO Barcode
(01)00303389777014

Carton Label

For Intravenous Infusion Use:
Dilute to a concentration of
2 mg/mL.

For Direct Injection Use: Dilute
to a concentration of 20 mg/mL.

See Prescribing Information
for a list of diluents.

Recommended Dosage: See
prescribing information

Store vial refrigerated at 2°C to
8°C (36°F to 46°F).

For multiple-dose use.

Each mL contains 214 mg
cyclophosphamide monohydrate
equivalent to 200 mg of
cyclophosphamide USP, and
83.9% (v/v) dehydrated alcohol
USP.

The container closure is not
made with natural rubber latex.

NDC 0338-9777-01

Cyclophosphamide
Injection
500 mg/2.5 mL
(200 mg/mL)

Must Dilute Before Intravenous Use

Sterile, Nonpyrogenic
Preservative-free

Baxter Logo
Manufactured for:
Baxter Healthcare Corporation
Deerfield, IL 60015 USA

FPO Barcode
(01)20303389777018

NDC 0338-9777-01 Rx Only

Cyclophosphamide
Injection
500 mg/2.5 mL
(200 mg/mL)

Must Dilute Before
Intravenous Use

HAZARDOUS DRUG

Multiple-Dose Vial

Refrigerate

NVCP500VUS 07-04-00-1281

NDC 0338-9777-01

Cyclophosphamide
Injection
500 mg/2.5 mL
(200 mg/mL)

Must Dilute Before
Intravenous Use

Sterile, Nonpyrogenic
Preservative-free

Baxter Logo
Manufactured for:
Baxter Healthcare Corporation
Deerfield, IL 60015 USA

Container Label

NDC 0338-9779-01

Cyclophosphamide
Injection
1,000 mg/5 mL
(200 mg/mL)

Must Dilute Before
Intravenous Use

HAZARDOUS DRUG

Rx Only Multiple Dose Vial

Dosage: See prescribing information.
Each mL contains 214 mg cyclo
phosphamide monohydrate equivalent
to 200 mg of cyclophosphamide USP.

Store vial refrigerated at 2° to 8°C
(36° to 46°F).

Manufactured for:
Baxter Healthcare Corporation
Deerfield, IL 60015 USA

FPO Barcode
(01)00303389779018

Carton Label

For Intravenous Infusion Use:
Dilute to a concentration of
2 mg/mL.

For Direct Injection Use: Dilute
to a concentration of 20 mg/mL.

See Prescribing Information
for a list of diluents.

Recommended Dosage: See
prescribing information.

Store vial refrigerated at 2°C to
8°C (36°F to 46°F).

For multiple-dose use.

Each mL contains 214 mg
cyclophosphamide monohydrate
equivalent to 200 mg of
cyclophosphamide USP, and 83.9%
(v/v) dehydrated alcohol USP.

The container closure is not made
with natural rubber latex.

NDC 0338-9779-01

Cyclophosphamide
Injection
1,000 mg/5 mL
(200 mg/mL)

Must Dilute Before
Intravenous Use

Sterile, Nonpyrogenic
Preservative-free

Baxter Logo
Manufactured for:
Baxter Healthcare Corporation
Deerfield, IL 60015 USA

FPO Barcode
(01)20303389779012

NDC 0338-9779-01 Rx Only

Cyclophosphamide
Injection
1,000 mg/5 mL
(200 mg/mL)

Must Dilute Before
Intravenous Use

HAZARDOUS DRUG

Multiple-Dose Vial

Refrigerate

NVCP1000VUS 07-04-00-1282

NDC 0338-9779-01

Cyclophosphamide
Injection
1,000 mg/5 mL
(200 mg/mL)

Must Dilute Before
Intravenous Use

Sterile, Nonpyrogenic
Preservative-free

Baxter Logo
Manufactured for:
Baxter Healthcare Corporation
Deerfield, IL 60015 USA